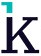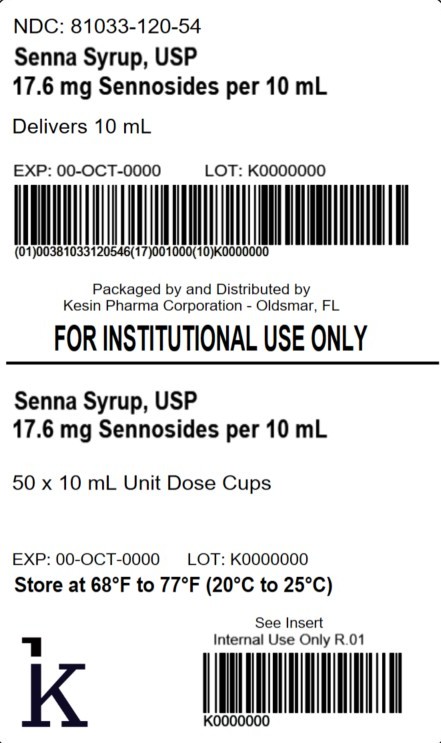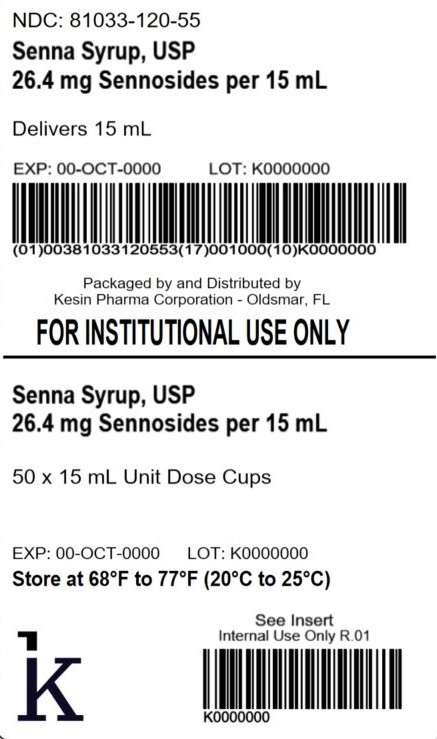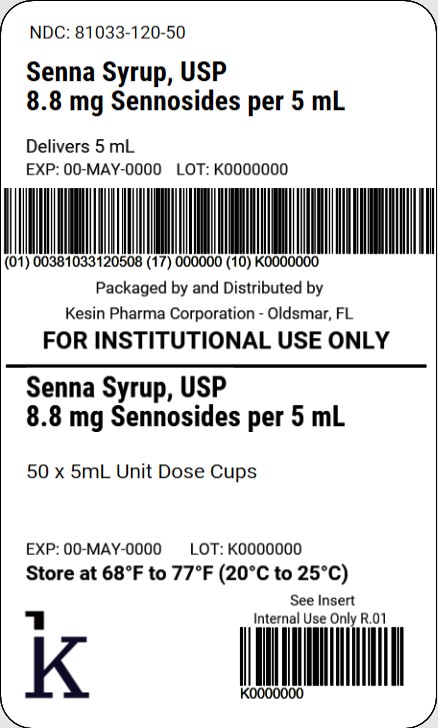 DRUG LABEL: Senna Syrup
NDC: 81033-120 | Form: SYRUP
Manufacturer: Kesin Pharma Corporation
Category: otc | Type: HUMAN OTC DRUG LABEL
Date: 20251014

ACTIVE INGREDIENTS: SENNOSIDES 8.8 mg/5 mL
INACTIVE INGREDIENTS: POTASSIUM CITRATE; PROPYLPARABEN; METHYLPARABEN; PROPYLENE GLYCOL; CITRIC ACID; AMMONIUM GLYCYRRHIZATE; WATER; SORBITOL; SUCRALOSE

Senna Syrup, USP 8.8 mg Sennosides per 5 mL

Active ingredient (per 5 mL)

Sennosides 8.8 mg

Purpose

Laxative

Uses

- relieves occasional constipation (irregularity)
- generally produces bowel movement in 6 to 12 hours

Warnings

Do not use

- laxative products for longer than 1 week unless directed by a doctor

Ask a doctor before use if you have

- stomach pain
- nausea
- vomiting
- noticed a sudden change in bowel habits that has continued for more than 2 weeks

Stop use and ask a doctor if

- you have rectal bleeding or failure to have a bowel movement after use of a laxative.

These could be signs of a serious condition.

If pregnant or breast-feeding,

ask a health professional before use.

Keep out of reach of children.

OVERDOSAGE

In case of overdose, get medical help or contact a Poison Control Center right away.

Directions

- shake well before use
- do not exceed recommended dose

Age | Starting Dose | Maximun Dose
adults and children 12 years of age and over | 10 mL to 15 mL once a day preferably at bedtime; increase as needed or as recommended by a doctor | 15 mL in the morning and 15 mL at bedtime
children under 12 years of age | ask a doctor | ask a doctor

Other information

- store at 20°C to 25°C (68°F to 77°F). [See USP Controlled Room Temperature]
- protect from light and moisture
- a dark brown, cherry flavored syrup supplied in the following:

NDC 81033-120-05: 5 mL unit dose cup
NDC 81033-120-50: Carton containing 50 unit-dose cups of 5 mL each

NDC 81033-120-10: 10 mL unit dose cup
NDC 81033-120-54: Carton containing 50 unit-dose cups of 10 mL each

NDC 81033-120-15: 15 mL unit dose cup
NDC 81033-120-55: Carton containing 50 unit-dose cups of 15 mL each

Inactive ingredients

cherry flavor, citric acid, methylparaben, monoammonium glycyrrhizinate, potassium citrate, propylene glycol, propylparaben, purified water, sorbitol, sucralose

Questions or comments?

Call 1-833-537-4679

Packaged by:
Kesin Pharma
Oldsmar, FL 34677
Rev. 10/2025

PIS-120-V02

PACKAGE LABEL

NDC 81033-120-50

Senna Syrup, USP

8.8 mg Sennosides per 5 mL

Delivers 5 mL

FOR INSTITUTIONAL USE ONLY

PACKAGE LABEL

NDC: 81033-120-54

Senna Syrup, USP

17.6 mg Sennosides per 10 mL

Delivers 10 mL

50 x 10 mL Unit Dose Cups

PACKAGE LABEL

NDC: 81033-120-55

Senna Syrup, USP

26.4 mg Sennosides per 15 mL

Delivers 15 mL

50 x 15 mL Unit Dose Cups